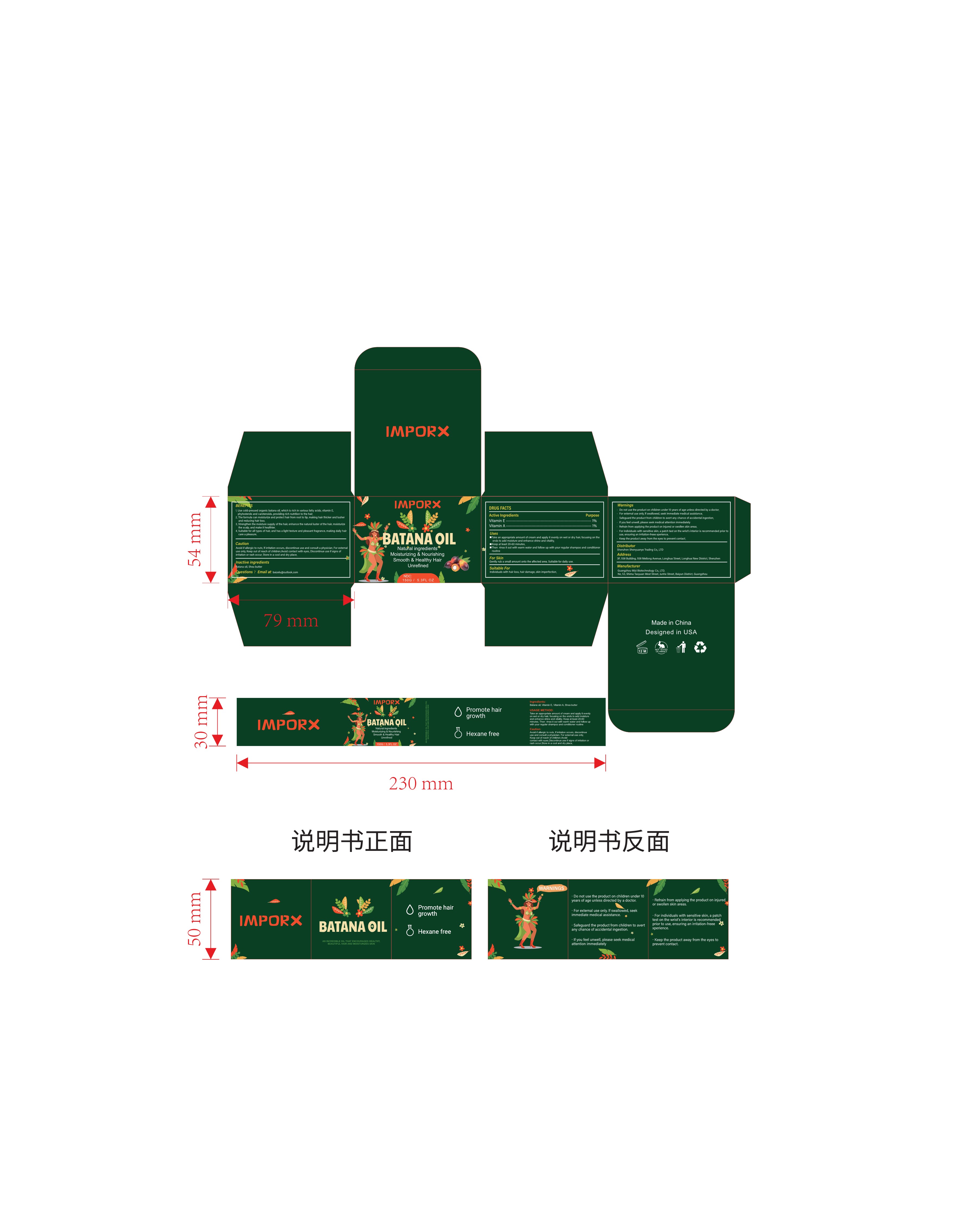 DRUG LABEL: Batana oil  hair care cream
NDC: 84336-001 | Form: CREAM
Manufacturer: Shenzhen Shenyuanye Trading Co., LTD
Category: otc | Type: HUMAN OTC DRUG LABEL
Date: 20240517

ACTIVE INGREDIENTS: VITAMIN A 1 g/100 g; .ALPHA.-TOCOPHEROL 1 g/100 g
INACTIVE INGREDIENTS: PALM OIL; SHEA BUTTER

巴塔纳油护发霜

ACTIVE INGREDIENT

Vitamin E------1%
Vitamin A------1%

PURPOSE

1. Use cold-pressed organic batana oil, which is rich in various fatty acids, vitamin E,phytosterols and carotenoids, providing rich nutrition to the hair.

2. The formula can moisturize and protect hair from root to tip, making hair thicker and lusherand reducing hair loss.

3. Strengthen the moisture supply of the hair, enhance the natural luster of the hair, moisturizthe scalp, and make it healthier,
4. Suitable for all types of hair, and has a light texture and pleasant fragrance, making daily hacare a pleasure.

INDICATIONS AND USAGE

Suitable For

Individuals with hair loss, hair damage, skin imperfection.

Take an appropriate amount of cream and apply it evenly on wet or dry hair, focusing on theends to add moisture and enhance shine and vitality.

Keep at least 20-60 minutes.

Then rinse it out with warm water and follow up with your regular shampoo and conditioner

Warnings

Do not use the product on children under 10 years of age unless directed by a doctor.

For external use only. If swallowed, seek immediate medical assistance.

Safeguard the product from children to avert any chance of accidental ingestion.

lf you feel unwell, please seek medical attention immediately.

For externaluse only.

DO NOT USE

Refrain from applying the product on injured or swollen skin areas.

WHEN USING

For individuals with sensitive skin, a patch test on the wrist's interior is recommended prior touse, ensuring an irritation-freee xperience.
Keep the product away from the eyes to prevent contact.

STOP USE

Avoid if allergic to nuts, lf irritation occurs, discontinue use and consult a physician.

Avoid contact with eyes. Discontinue use if signs ofirritation or rash occur.

Keep out of reach of children

DOSAGE AND ADMINISTRATION

For Skin
Gently rub a small amount onto the affected area. Suitable for daily use.

INACTIVE INGREDIENT

Batana oil, Shea butter

QUESTIONS

Email at: baizelu@outlook.com